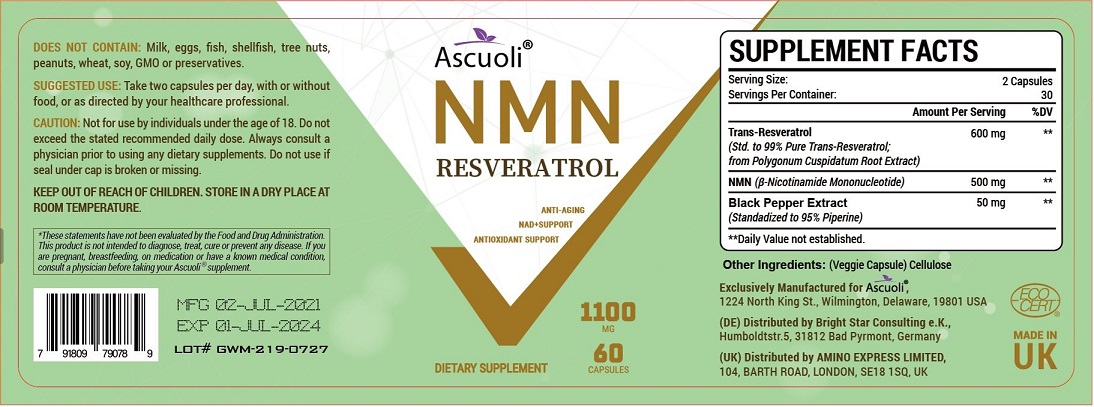 DRUG LABEL: Ascuoli
NDC: 83459-001 | Form: CAPSULE
Manufacturer: HEALGROW INC
Category: otc | Type: HUMAN OTC DRUG LABEL
Date: 20230526

ACTIVE INGREDIENTS: RESVERATROL 600 mg/1 1; NICOTINAMIDE MONONUCLEOTIDE 500 mg/1 1; WHITE PEPPER 50 mg/1 1
INACTIVE INGREDIENTS: POWDERED CELLULOSE

Active ingredient

Resveratrol 600mg

β-Nicotinamide Mononucleotide 500mg

Piper nigrum extract 50mg

Warning

Not for use by individuals under the age of 18. Do not exceed the stated recommended daily dose. Always consult a physician prior to using any dietary supplements. Do not use if seal under cap is broken or missing.

Direction

Take two capsules per day, with or without food, or as direacted by your healthcare professional.

Inactive ingredient

Cellulose (Veggie Capsule)

Other information

Store in a dry place at room temperature